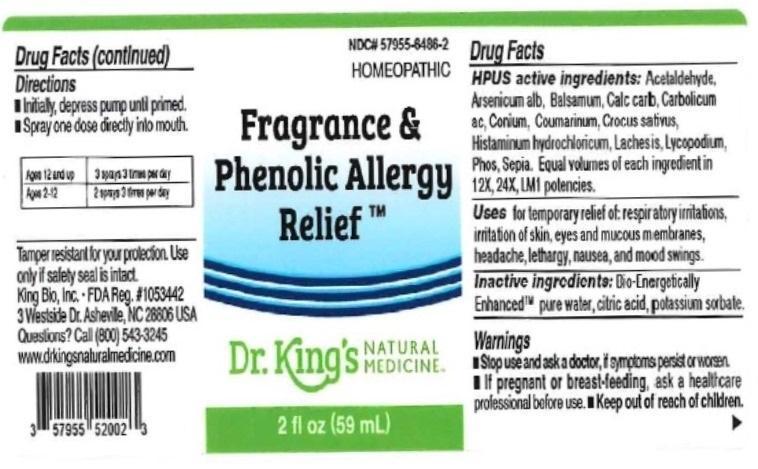 DRUG LABEL: Fragrance and Phenolic Allergy Relief
NDC: 57955-6486 | Form: LIQUID
Manufacturer: King Bio Inc.
Category: homeopathic | Type: HUMAN OTC DRUG LABEL
Date: 20160318

ACTIVE INGREDIENTS: ACETALDEHYDE 12 [hp_X]/59 mL; ARSENIC TRIOXIDE 12 [hp_X]/59 mL; BALSAM PERU 12 [hp_X]/59 mL; OYSTER SHELL CALCIUM CARBONATE, CRUDE 12 [hp_X]/59 mL; CONIUM MACULATUM FLOWERING TOP 12 [hp_X]/59 mL; COUMARIN 12 [hp_X]/59 mL; SAFFRON 12 [hp_X]/59 mL; HISTAMINE DIHYDROCHLORIDE 12 [hp_X]/59 mL; LACHESIS MUTA VENOM 12 [hp_X]/59 mL; LYCOPODIUM CLAVATUM SPORE 12 [hp_X]/59 mL; PHOSPHORUS 12 [hp_X]/59 mL; SEPIA OFFICINALIS JUICE 12 [hp_X]/59 mL
INACTIVE INGREDIENTS: WATER; ANHYDROUS CITRIC ACID; POTASSIUM SORBATE

Fragrance and Phenolic Allergy Relief™

ACTIVE INGREDIENT

Drug Facts__________________________________________________________________________________________________________

HPUS active ingredients: Acetaldehyde, Arsenicum album, Balsamum peruvianum, Calcarea carbonica, Carbolicum acidum, Conium maculatum, Coumarinum, Corcus sativus, Histaminum hydrochloricum, Lachesis mutus, Lycopodium clavatum, Phosphorus, Sepia. Equal volumes of each ingredient in 12X, 24X, and LM1 potencies.

INDICATIONS AND USAGE

Uses for temporary relief of: respiratory irritations, irritation of skin, eyes and mucous membranes, headache, lethargy, nausea, mood swings.

Inactive Ingredients:

Bio-Energetically Enhanced™ pure water, citric acid and potassium sorbate.

Warnings

- Stop use and ask your doctor if symptoms persist or worsen.
- If pregnant or breast-feeding, ask a healthcare professional before use.

- Keep out of reach of children.

Directions

- Initially, depress pump until primed.
- Spray one dose directly into mouth.
- Ages 12 and up: 3 sprays 3 times per day.
- Ages 2-12 years: 2 sprays 3 times per day.

OTHER SAFETY INFORMATION

Tamper resistant for your protection. Use only if safety seal is intact.

PURPOSE

Uses for temporary relief of:

- respiratory irritations
- irritation of skin, eyes and mucous membranes
- headache
- lethargy
- nausea
- mood swings

PACKAGE LABEL

*z

kjhgfdsawertyuiop[]\